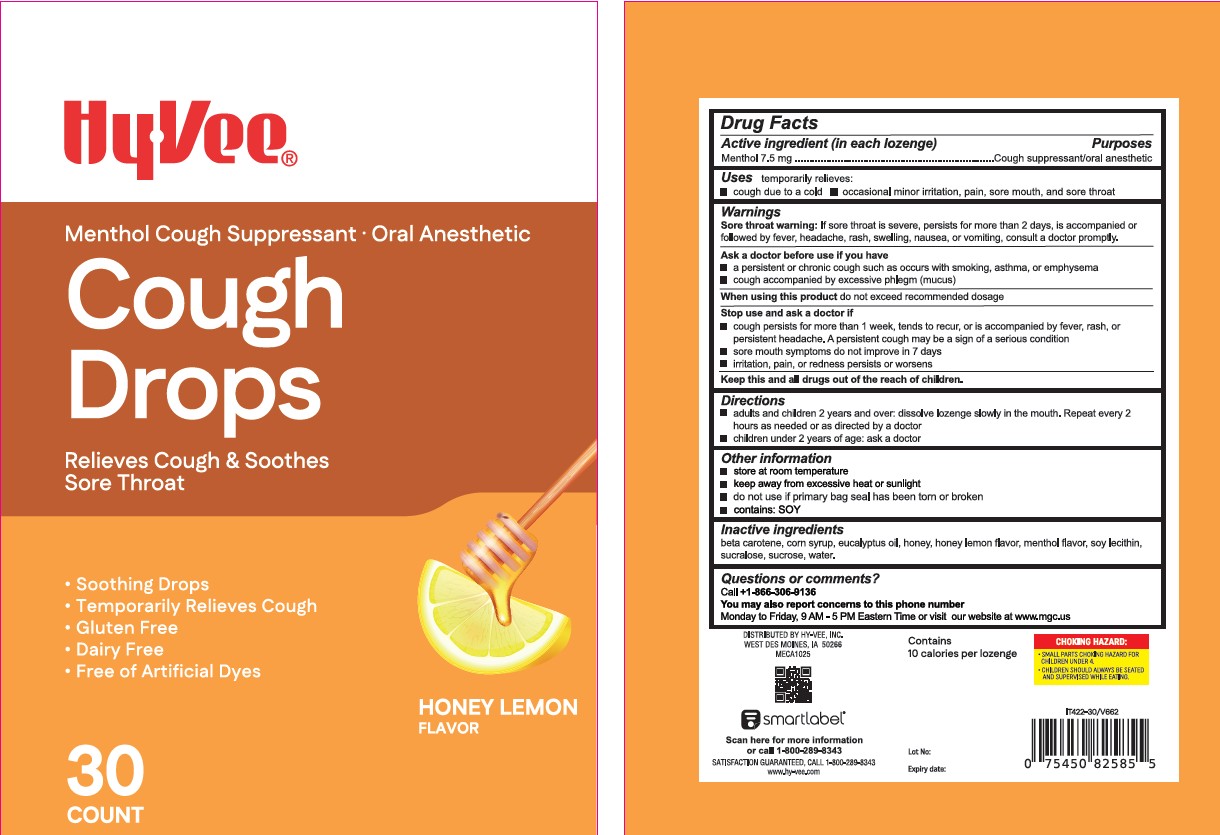 DRUG LABEL: HyVee Cough Drops Honey Lemon
NDC: 42507-904 | Form: LOZENGE
Manufacturer: HY-VEE, INC
Category: otc | Type: HUMAN OTC DRUG LABEL
Date: 20260105

ACTIVE INGREDIENTS: MENTHOL 7.5 mg/1 1
INACTIVE INGREDIENTS: BETA CAROTENE; CORN SYRUP; EUCALYPTUS OIL; HONEY; LECITHIN, SOYBEAN; SUCRALOSE; SUCROSE; WATER

Xiamen-Hyvee Cough Drops Honey Lemon 30

Active Ingredient(s)

Menthol 7.5 mg

Purpose

Purposes cough suppressant, oral anesthetic

Use

temporary relieves: ■ cough due to cold ■ occasional minor irritation or sore throat

Warnings

Sore throat warning: If sore throat is severe, persists for more than 2 days, is accompanied or follow headache, rash, swelling, nausea, or vomiting, consult a doctor promptly.

Ask a doctor before use if you have: ■ persistent or chronic cough such as occurs with smoking, asthma, or emphysema ■ cough accompanied by excessive phlegm (mucus).

Stop use and ask a doctor if ■ cough persists for more than 1 week, tends to recur, or is accompained by fever, rash, or persistent headache. These could be signs of a serius condition. ■ sore mouth does not improve in 7 days ■ irritation, pain, or redness persists or worsens.

KEEP OUT OF REACH OF CHILDREN

Keep this and all drugs out of reach of children

Directions

■ adults and children 2 years and over: dissolve lozenge slowly in the mouth. Repeat every 2 hours as needed or directed by doctor.

■ children under 2 years: ask a doctor.

Other information

■ store at room temperature ■ Keep away from excessive heat or sunlight ■ do not use if primary bag seal has been torn or broken ■ contains: SOY.

Inactive ingredients

BETA CAROTENE, CORN SYRUP, EUCALYPTUS OIL, HONEY, HONEY LEMON FLAVOR, MENTHOL FLAVOR, SOY LECITHIN, SUCRALOSE, SUCROSE, WATER

QUESTIONS

Call +1-866-306-9136

You may also report concerns to this phone number

Monday to Friday, 9 AM - 5 PM Eastern Time or visit our website at www.mgc.us